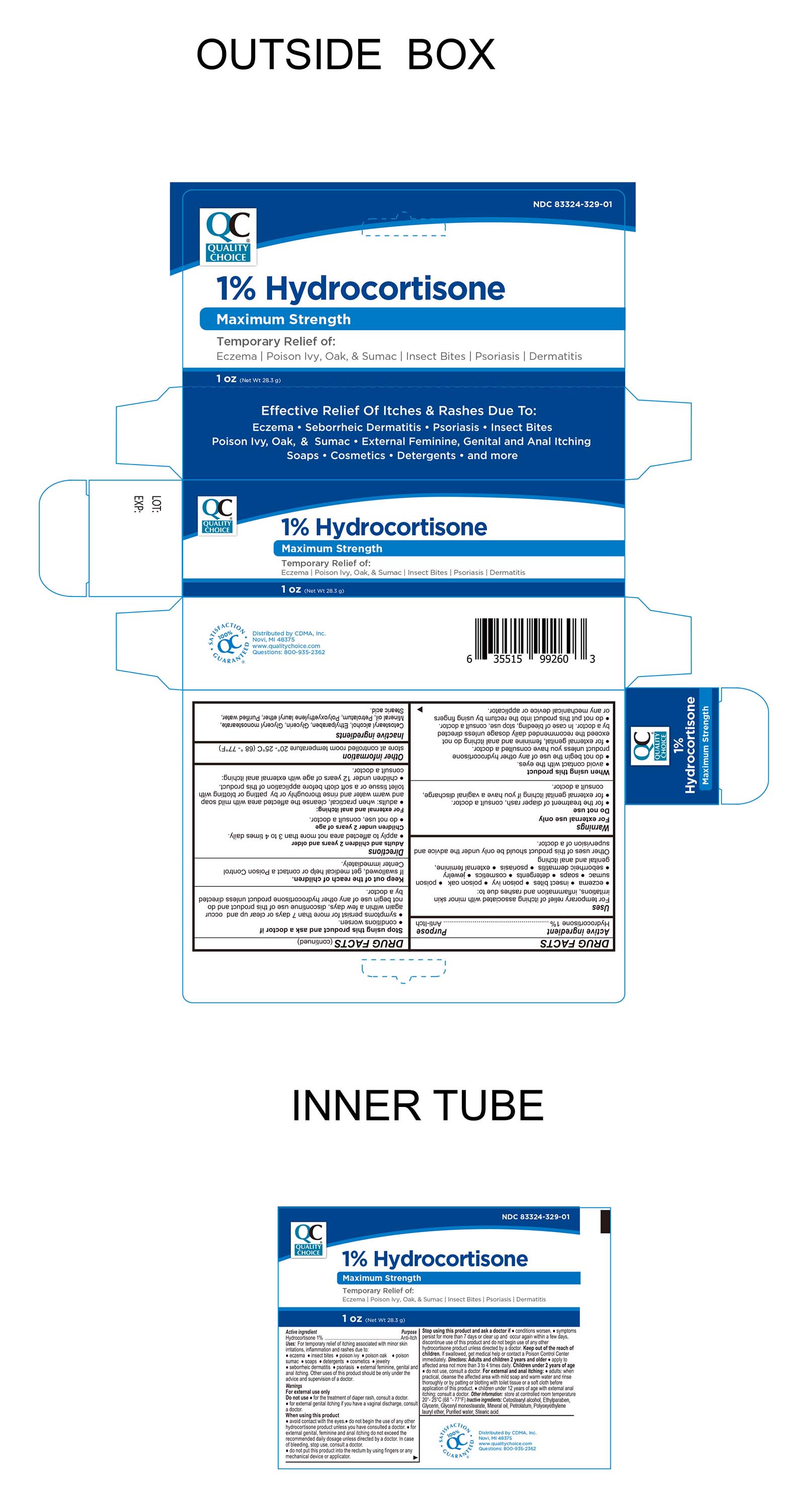 DRUG LABEL: Hydrocortisone 1%
NDC: 83324-329 | Form: CREAM
Manufacturer: Chain Drug Marketing Association Inc.
Category: otc | Type: HUMAN OTC DRUG LABEL
Date: 20250929

ACTIVE INGREDIENTS: HYDROCORTISONE 1 g/100 g
INACTIVE INGREDIENTS: SODIUM LAURETH-4 PHOSPHATE; GLYCERIN; STEARIC ACID; GLYCERYL MONOSTEARATE; PETROLATUM; ETHYLPARABEN; CETOSTEARYL ALCOHOL; WATER; MINERAL OIL

Quality Choice Hydrocortisone Cream 1%
MAXIMUM STRENGTH

Active ingredient

Hydrocortisone 1%

Purpose

Anti-Itch

Keep out of the reach of children.

If swallowed, get medical help or contact a Poison Control Center immediately.

Uses

For temporary relief of itching associated with minor skin irritations, inflammation and rashes due to:

● eczema ● seborrheic dermatitis ● psoriasis ● insect bites ● poison ivy, oak, sumac ● soaps

● detergents ● cosmetics ● jewelry ● external feminine genital and anal itching

Other uses of this product should be only under the advice and supervision of a doctor

Warnings

For external use only

Do not Use:

For the treatment of a diaper rash, consult with doctor

For external genital itching if you have a vaginal discharge, consult doctor

When using this product

- Avoid Contact with the eyes
- Do not begin the use of any other hydrocortisone product unless you have consulted a doctor
- For external genital, feminine and anal itching do not exceed the recommended daily dosage unless directed by a doctor. In case of bleeding, stop use and consult a doctor.
- do not put this product into the rectum by using fingers or any medicated device or applicator.

Stop using this product and ask a doctor if

- conditions worsen
- symptoms persist for more than 7 days or clear up and occur again within a few days, discontinue use of this product and do not begin use of any other hydrocortisone product unless directed by a doctor.

Directions

Adults and children 2 years of age and older: apply to the affected area not more than 3 to 4 times daily.

Children under 2 years of age: do not use, consult a doctor.

For External and anal itching:

Adults: When practical, cleanse the affected area with mild soap and warm water and rinse thoroughly or by patting or blotting with toilet tissue or a soft cloth before application of this product.

Children: under 12 years of age with external anal itching: consult a doctor.

Inactive ingredients

Cetostearyl alcohol, Ethylparaben, Glycerin, Glyceryl monostearate, Mineral Oil, Petrolatum, Polyoxyethylene lauryl ether, Purified Water, Stearic Acid.

Other information

● store at controlled room temperature 20°-25°C (68 °- 77 °F)

Distributed by: CDMA, Inc.

Novi, MI. 48375

www.qualitychoice.com

Questions: 800-935-2362